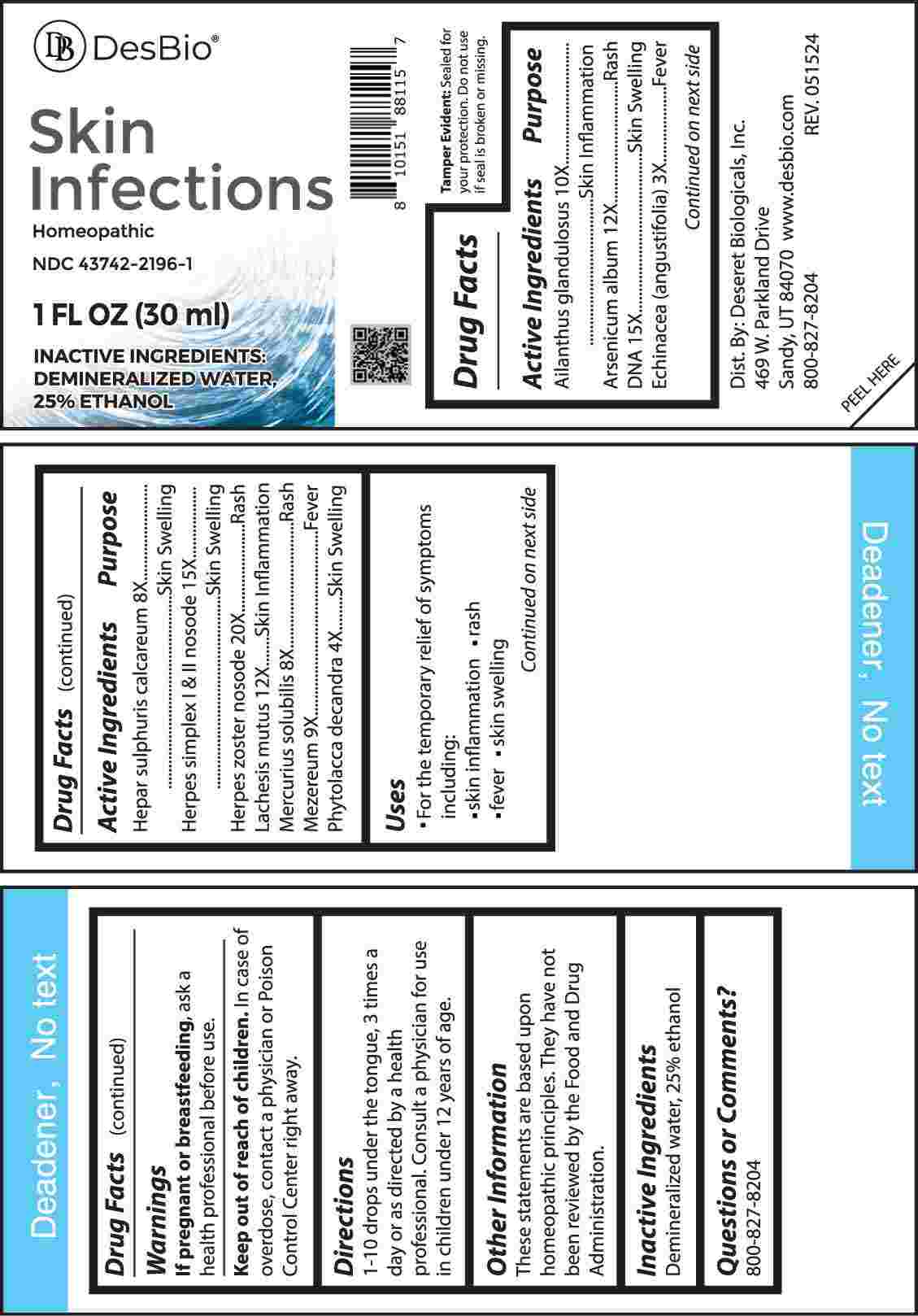 DRUG LABEL: Skin Infections
NDC: 43742-2196 | Form: LIQUID
Manufacturer: Deseret Biologials, Inc.
Category: homeopathic | Type: HUMAN OTC DRUG LABEL
Date: 20240830

ACTIVE INGREDIENTS: AILANTHUS ALTISSIMA FLOWERING TWIG 10 [hp_X]/1 mL; ARSENIC TRIOXIDE 12 [hp_X]/1 mL; HERRING SPERM DNA 15 [hp_X]/1 mL; ECHINACEA ANGUSTIFOLIA WHOLE 3 [hp_X]/1 mL; CALCIUM SULFIDE 8 [hp_X]/1 mL; HUMAN HERPESVIRUS 1 15 [hp_X]/1 mL; HUMAN HERPESVIRUS 2 15 [hp_X]/1 mL; HUMAN HERPESVIRUS 3 20 [hp_X]/1 mL; LACHESIS MUTA VENOM 12 [hp_X]/1 mL; MERCURIUS SOLUBILIS 8 [hp_X]/1 mL; DAPHNE MEZEREUM BARK 9 [hp_X]/1 mL; PHYTOLACCA AMERICANA ROOT 4 [hp_X]/1 mL
INACTIVE INGREDIENTS: WATER; ALCOHOL

DRUG FACTS:

ACTIVE INGREDIENTS:

Ailanthus Glandulosus 10X, Arsenicum Album 12X, DNA 15X, Echinacea (Angustifolia) 3X, Hepar Sulphuris Calcareum 8X, Herpes Simplex I & II Nosode 15X, Herpes Zoster Nosode 20X, Lachesis Mutus 12X, Mercurius Solubilis 8X, Mezereum 9X, Phytolacca Decandra 4X.

PURPOSE:

Ailanthus Glandulosus – Skin Inflammation, Arsenicum Album - Rash, DNA – Skin Swelling, Echinacea (Angustifolia) - Fever, Hepar Sulphuris Calcareum – Skin Swelling, Herpes Simplex I & II Nosode – Skin Swelling, Herpes Zoster Nosode - Rash, Lachesis Mutus – Skin Inflammation, Mercurius Solubilis - Rash, Mezereum - Fever, Phytolacca Decandra – Skin Swelling

USES:

• For the temporary relief of symptoms including:

• skin inflammation • rash • fever • skin swelling

These statements are based upon homeopathic principles. They have not been reviewed by the Food and Drug Administration.

WARNINGS:

If pregnant or breast-feeding, ask a health professional before use.

Keep out of reach of children. In case of overdose, contact a physician or Poison Control Center right away.

Tamper Evident: Sealed for your protection. Do not use if seal is broken or missing.

KEEP OUT OF REACH OF CHILDREN:

In case of overdose, contact a physician or Poison Control Center right away.

DIRECTIONS:

1-10 drops under the tongue, 3 times a day or as directed by a health professional. Consult a physician for use in children under 12 years of age.

INACTIVE INGREDIENTS:

Demineralized water, 25% ethanol

QUESTIONS:

Dist. By: Deseret Biologicals, Inc.

469 W. Parkland Drive

Sandy, UT 84070 www.desbio.com

800-827-8204

PACKAGE LABEL DISPLAY:

DesBio

Skin Infections

Homeopathic

NDC 43742-2196-1

1 FL OZ (30 ml)